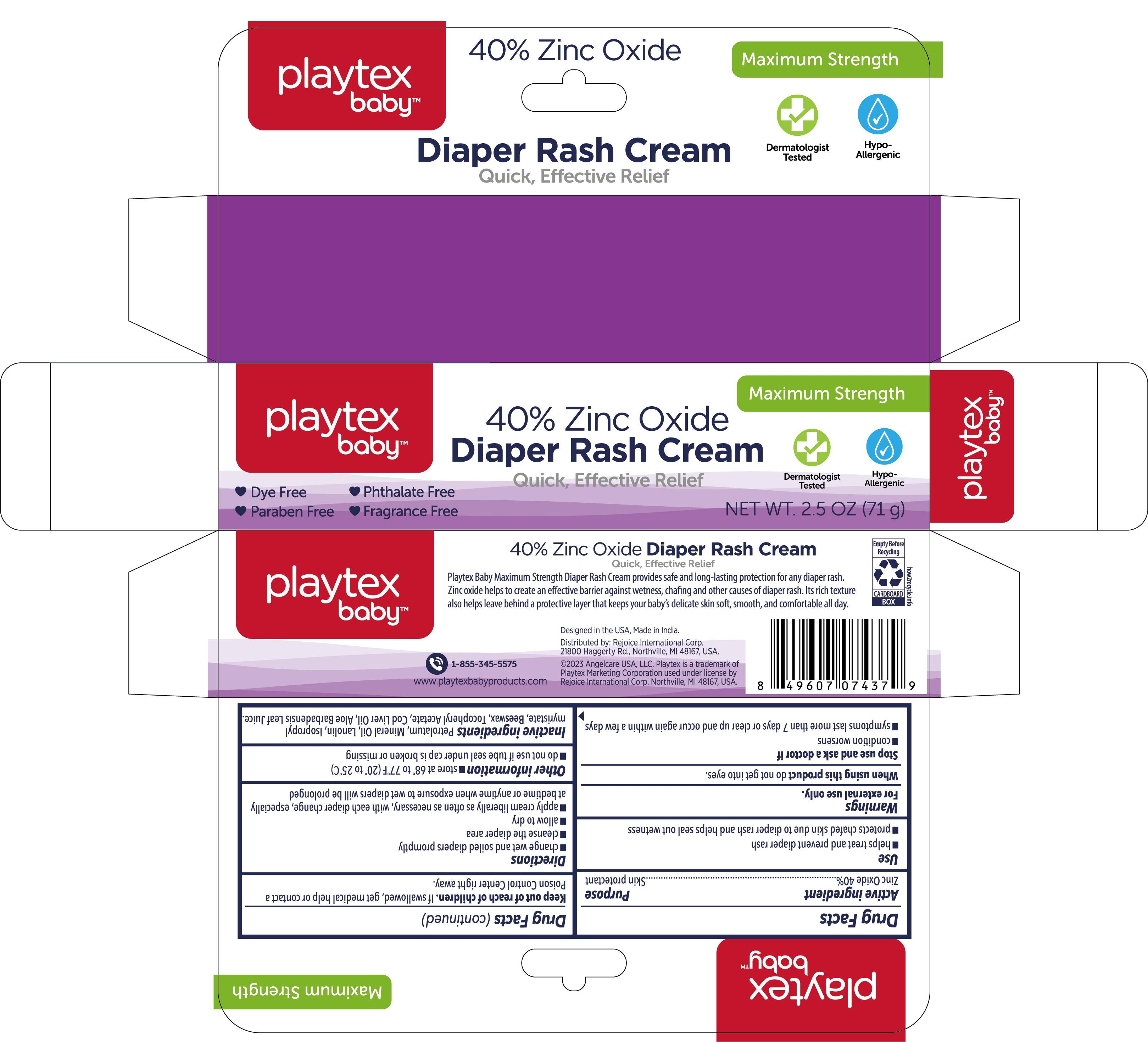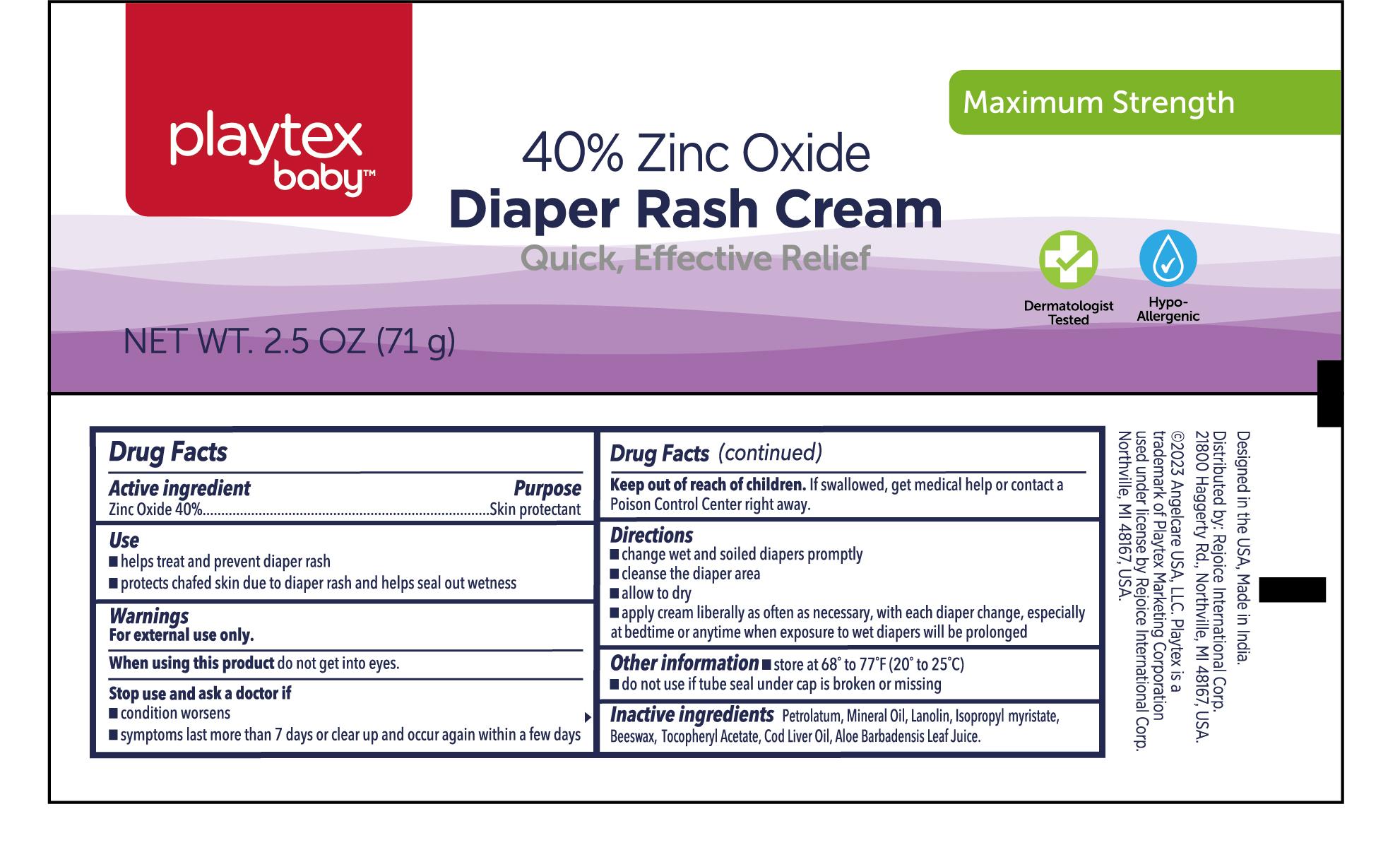 DRUG LABEL: Diaper Rash Cream 2.5oz
NDC: 57337-165 | Form: CREAM
Manufacturer: Rejoice International Corp.
Category: otc | Type: HUMAN OTC DRUG LABEL
Date: 20241021

ACTIVE INGREDIENTS: ZINC OXIDE 40 g/100 g
INACTIVE INGREDIENTS: COD LIVER OIL; PETROLATUM; MINERAL OIL; LANOLIN; ISOPROPYL MYRISTATE; YELLOW WAX; .ALPHA.-TOCOPHEROL ACETATE; ALOE VERA LEAF

DIAPER RASH CREAM 2.5OZ

Active ingredient

Zinc Oxide 40%

Purpose

Skin protectant

Use

- helps treat and prevent diaper rash. Protects chafed skin due to diaper rash and helps seal out wetness.

Warnings

Warnings: For external use only.

When using this product do not get into eyes.

Stop use and ask a doctor if

- condition worsens
- symtoms last more than 7 days or clear up and occur again within a few days.

Keep out of reach of children

- if swallowed, get medical help or contact a Poison Control Center right away.

Do not use if tube seal under cap is broken or missing

Directions

- change wet and soiled diapers promotly
- cleanse the diaper area
- allow to dry
- apply cream liberally as often as necessary, with each diaper change, especially at bedtime or anytime when exposure to wet diapers will be prolonged

Other information

- store at 68º to 77ºF (20º to 25ºC)
- do not use if tube seal under cap is broken or missing

Inactive ingredients

Petrolatum, Mineral Oil, Lanolin, Isopropyl Myristate, Beeswax, Tocopheryl Acetate, Cod Liver Oil, Aloe Barbadensis Leaf Juice